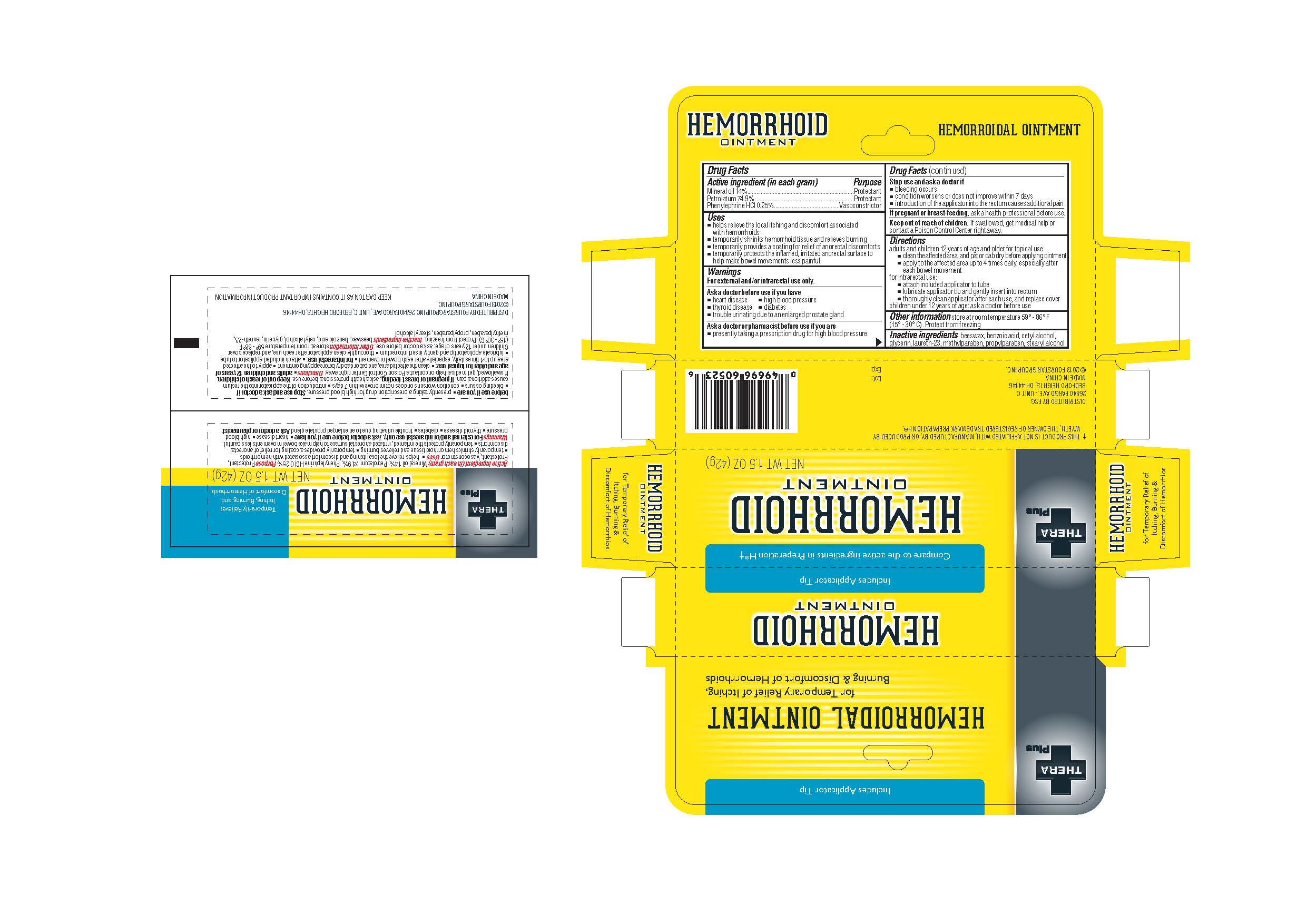 DRUG LABEL: 
                  TheraPlus				
                
                  

NDC: 55621-005 | Form: OINTMENT
Manufacturer: Zhejiang Jingwei Pharmaceutical Co., Ltd.
Category: otc | Type: HUMAN OTC DRUG LABEL
Date: 20231025

ACTIVE INGREDIENTS: PHENYLEPHRINE HYDROCHLORIDE 0.25 g/100 g; MINERAL OIL 14 g/100 g; PETROLATUM 74.9 g/100 g
INACTIVE INGREDIENTS: YELLOW WAX; BENZOIC ACID; CETYL ALCOHOL; GLYCERIN; LAURETH-23; METHYLPARABEN; PROPYLPARABEN; STEARYL ALCOHOL

Drug Facts

INACTIVE INGREDIENT

beeswax, benzoic acid, cetyl alcohol, glycerin, laureth-23, methylparaben, propylparaben, stearyl alcohol Inactive Ingredients

Active Ingredient (in each gram)

Mineral oil 14%

Petrolatum 74.9%

Phenylephrine HCI 0.25%

Warnings

For external and/or intrarectal use only

Purpose

Protectant

Protectant

Vasoconstrictor

KEEP OUT OF REACH OF CHILDREN

. If swallowed, get medical help or contact a Poison Control Center right away. Keep out of reach of children

Uses

-helps relieve the local itching and discomfort associated with hemorrhoids

-temporarily shrinks hemorrhoid tissue and relieves burning

-temporarily provides a coating for relief of anorectal discomforts

-temporarily protects the inflamed, irritated anorectal surface to help make bowel movements less painful

Directions

adults and children 12 years of age and older for topical use:

-clean the affected area, and oat or dab dry before applying ointment

-apply to the affected area up to 4 times daily, especially after each bowel movement

for intrarectal use:

-attach included applicator to tube

-lubricate applicator tip and gently insert into rectum

-thoroughly clean applicator after each use, and replace cover

children under 12 years of age: ask a doctor before use

PREGNANCY OR BREAST FEEDING

, ask a health professional before use If pregnant or breast-feeding

Stop use and ask a doctor if

-bleeding occurs

-condition worsens or does not improve within 7 days

-introduction of the applicator into the rectum causes additional pain

Ask a doctor before use if you have

-heart disease

-high blood pressure

-thyroid disease

-diabetes

-trouble urinating due to an enlarged prostate gland

Ask a doctor or pharmacist before use if you are

-presently taking a prescription drug for high blood pressure